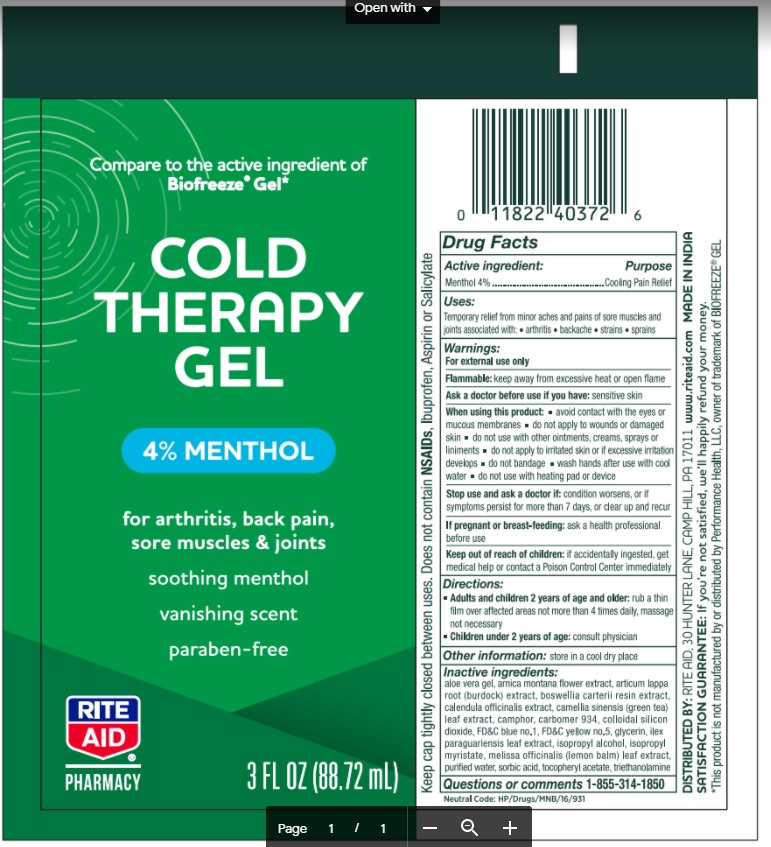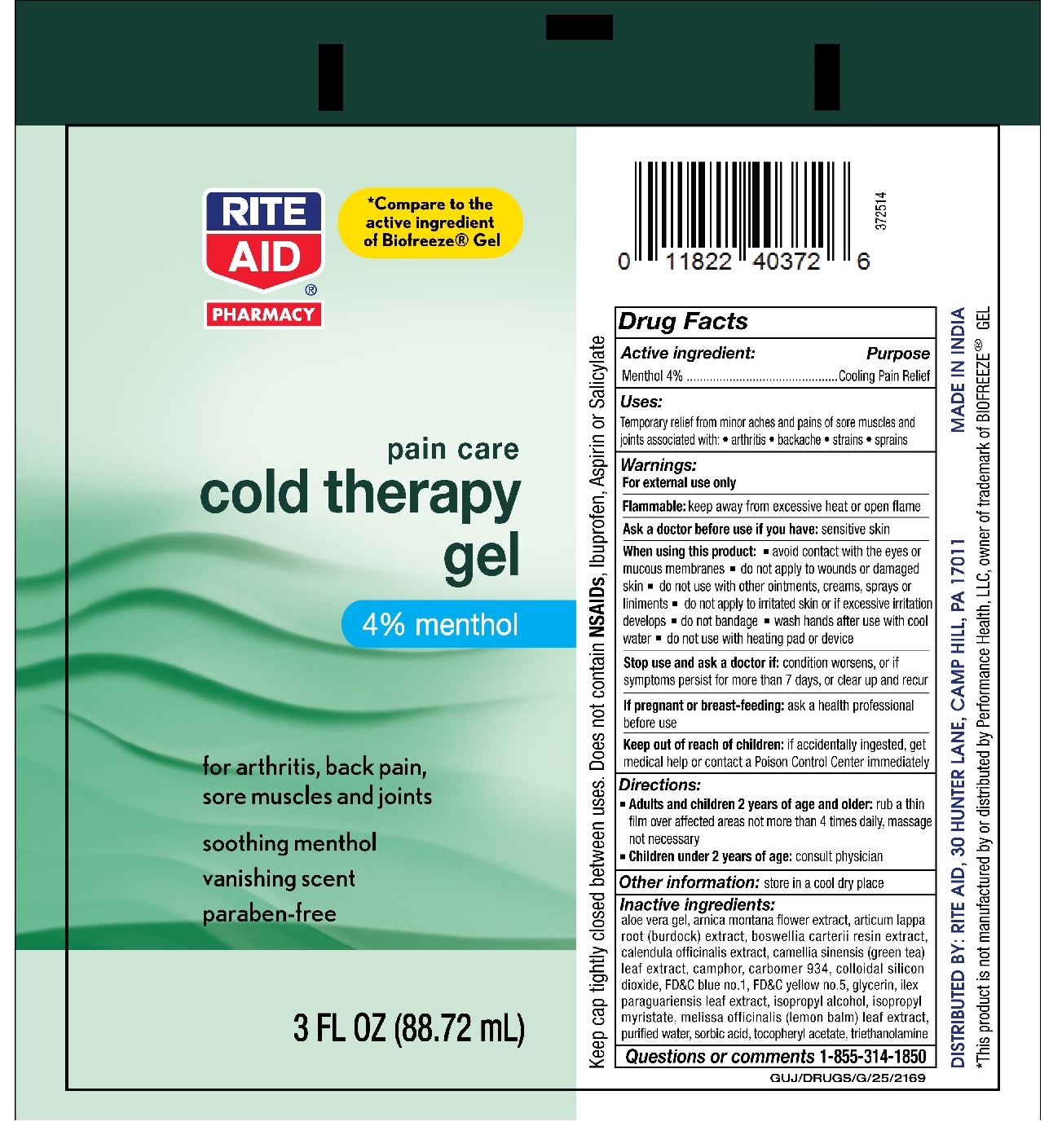 DRUG LABEL: Cold Zone Pain Relieving Gel- Rite Aid
NDC: 76168-314 | Form: GEL
Manufacturer: Velocity Pharma LLC
Category: otc | Type: HUMAN OTC DRUG LABEL
Date: 20201005

ACTIVE INGREDIENTS: MENTHOL 40 mg/1 mL
INACTIVE INGREDIENTS: CAMPHOR (NATURAL); BRILLIANT BLUE G; PETROLATUM; CARBOXYPOLYMETHYLENE; ALOE VERA LEAF; ARNICA MONTANA FLOWER; ARCTIUM LAPPA WHOLE; CALENDULA OFFICINALIS FLOWER; FRANKINCENSE; GREEN TEA LEAF; ILEX PARAGUARIENSIS LEAF; MELISSA OFFICINALIS LEAF; ISOPROPYL ALCOHOL; ISOPROPYL MYRISTATE; .ALPHA.-TOCOPHEROL ACETATE; SILICON DIOXIDE; TROLAMINE; SORBIC ACID; WATER; FD&C BLUE NO. 1; FD&C YELLOW NO. 5

Cold Zone Pain Relieving Gel- Rite Aid

Active Ingredients

Menthol USP 4%

Purpose

Cooling Pain Relief

Uses

Temporary relief from minor aches and pains of sore muscles and joints associated with: - arthritis - backache - strains - sprains

Warnings:

For external use only

Flammable:

Keep away from excessive heat or open flame.

Ask a doctor before use if you have:

sensitive skin

When using this product:

- Avoid contact with the eyes or mucous membranes
- Do not apply to wounds or damaged skin
- Do not use with other ointments, creams, sprays or liniments
- Do not apply to irritated skin or if excessive irritated develops
- Do not bandage
- Wash hands after use with cool water
- Do not use with heating pad or device

Stop use and ask a doctor if:

Condition worsens, or if symptoms persist for more than 7 days, or clear up and recur

If pregnant or breast-feeding:

Ask a health professional before use

Keep out of reach of children:

If accidentally ingested, get medical help or contact a Poison Control Center immediately

Directions:

- Adults and children 2 years of age and older: Rub a thin film over affected areas not more than 4 times daily; massage not necessary
- Children under 2 years of age: Consult physician

Other Information:

Store in a cool dry place with lid closed tightly.

Questions or Comments - Call 1-855-314-1850

Inactive Ingredients

Purified water, Glycerin, Isopropyl alcohol, Iso propyl myristate, Carbopol usp, Aloevera gel, Arnica montana flower extract, Articum lappa root (burdock) extract, Boswellia carterii resin extract, Calendula officinalis extract, Camellia sinensis leaf extract, camphorm934, colloidal silicon dioxide, FD&C blue no. 1, FD&C yellow no. 5, glycerin, Iiex paraguariensis leaf extract, Isopropyl alchohol, Isopropyl myristate, Melissa officinalis (lemon balm) leaf extract, Tocopheryl acetate, Triethanolamine, Sorbic acid.